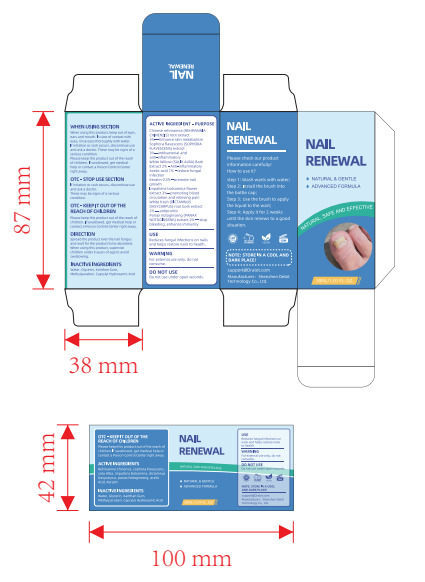 DRUG LABEL: NAIL RENEWAL
NDC: 83619-003 | Form: LIQUID
Manufacturer: Shenzhen Derbit Technology Co., Ltd.
Category: otc | Type: HUMAN OTC DRUG LABEL
Date: 20240508

ACTIVE INGREDIENTS: WILLOW BARK 2 g/100 mL; IMPATIENS BALSAMINA WHOLE 3 g/100 mL; HAIR KERATIN AMINO ACIDS 0.5 g/100 mL; ACETIC ACID 1 g/100 mL; DICTAMNUS DASYCARPUS WHOLE 2 g/100 mL; LIPPIA REHMANNII WHOLE 3 g/100 mL; SOPHORA FLAVESCENS WHOLE 3 g/100 mL; PANAX NOTOGINSENG WHOLE 2 g/100 mL
INACTIVE INGREDIENTS: WATER; GLYCERIN; CAPRYLHYDROXAMIC ACID; XANTHAN GUM; METHYLPARABEN

83619-003

Active Ingredient(s)

REHMANNIA CHINENSIS：3%

SOPHORA FLAVESCENS：3%

SALIX ALBA：2%

acetic acid：1%

Keratin：0.5%

IMPATIENS BALSAMINA：3%

DICTAMNUS DASYCARPUS：2%

PANAX NOTOGINSENG：2%

Purpose

Chinese rehmannia (REHMANNIA CHINENSIS) root extract 3%- - - -Enhance skin metabolism
Sophora flavescens (SOPHORA FLAVESCENS) extract 3%-antibacterial and anti-inflammatory
White Willow (SALIX ALBA) Bark Extract 2% - Anti-inflammatory Acetic acid 1% - reduce fungal
infection Keratin 0.5%- -promote nail growth Impatiens balsamina flower extract 3%--promoting blood
circulation and relieving pain White fresh (DICTAMNUS DASYCARPUS) root bark extract
2% - antipruritlc Panax notoginseng (PANAX NOTOGINSENG) extract 2% -- stop
bleeding, enhance immunity

Use

Reduces fungal infections on nails and helps restore nails to health.

Warnings

For external use only, do not consume.

Do not use under open wounds.

When using this product, keep out of eyes, ears and mouth. In case of contact with eyes, rinse eyes thoroughly with water.
If rritatioin or rash occurs, discontinue use and ask a doctor. These may be signs of a serious condition. Please keep this

product out of the reach of children. If swallowed, get medical help or contact a Poison Control Center right away.

STOP USE

If iritation or rash occurs, discontinue use and ask a doctor. These may be signs of a serious condition.

KEEP OUT OF REACH OF CHILDREN

Please keep this product out of the reach of children. If swallowed, get medical help or
contact a Poison Control Center right away.

Directions

Spread the product over the nail fungus and walt for the product to be absorbed.
When using this product, supervise children under 6 years of age to avoid
swallowing.

Other information

No data available

Inactive ingredients

Water, Glycerin, Xanthan Gum, Methylparaben, Caprylyl Hydroxamic Acid